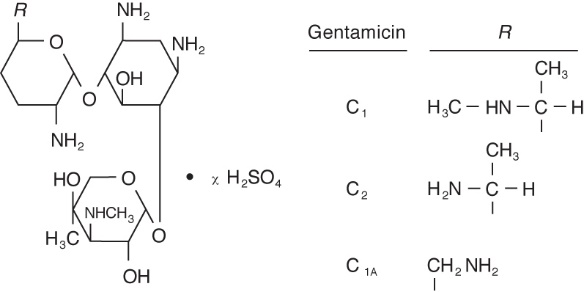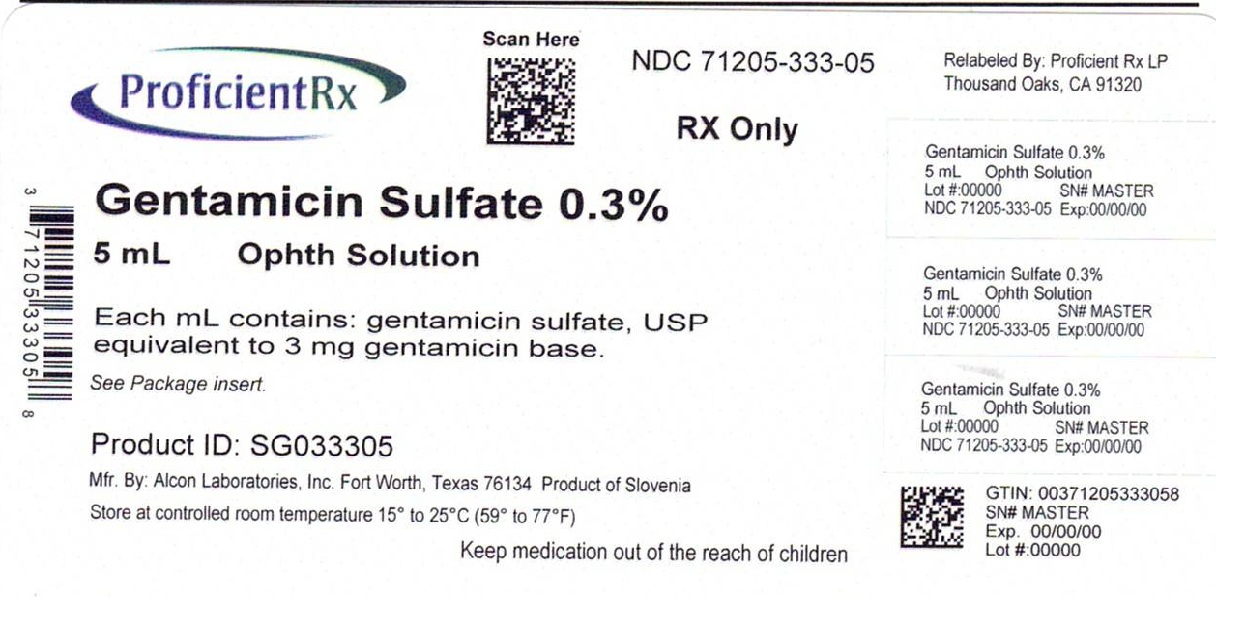 DRUG LABEL: Gentamicin Sulfate
NDC: 71205-333 | Form: SOLUTION
Manufacturer: Proficient Rx LP
Category: prescription | Type: HUMAN PRESCRIPTION DRUG LABEL
Date: 20250501

ACTIVE INGREDIENTS: GENTAMICIN SULFATE 3 mg/1 mL
INACTIVE INGREDIENTS: BENZALKONIUM CHLORIDE; SODIUM CHLORIDE; SODIUM PHOSPHATE; TYLOXAPOL; SODIUM HYDROXIDE; HYDROCHLORIC ACID; WATER

Gentamicin Sulfate
Ophthalmic Solution USP

Sterile

DESCRIPTION: Gentamicin Sulfate is a water-soluble antibiotic of the aminoglycoside group. Gentamicin Sulfate Ophthalmic Solution is a sterile, aqueous solution buffered to approximately pH 7 for ophthalmic use. Gentamicin is obtained from cultures of Micromonospora purpurea. It is a mixture of the sulfate salts of gentamicin C1, C2, and C1A. All three components appear to have similar antimicrobial activities. Gentamicin sulfate occurs as white powder and is soluble in water and insoluble in alcohol. The structure is as follows:

Established name: Gentamicin Sulfate

Chemical name: 0-3-Deoxy-4-C-methyl-3-(methylamino)-β-L-arabinopyranosyl-(1→6)-0-[2,6-diamino-2,3,4,6-tetradeoxy-α-D-erythro-hexopyranosyl-(1→4)]-2-deoxy-D-streptamine.

Ingredients: Each mL contains: Active: Gentamicin Sulfate USP (equivalent to 3 mg gentamicin). Preservative: Benzalkonium Chloride 0.1 mg (0.01%). Inactives: Sodium Chloride, Dried Sodium Phosphate, Tyloxapol, Sodium Hydroxide and/or Hydrochloric Acid (to adjust pH) and Purified Water.

CLINICAL PHARMACOLOGY

CLINICAL PHARMACOLOGY: Microbiology: Gentamicin sulfate is active in vitro against many strains of the following microorganisms:

Staphylococcus aureus, Staphylococcus epidermidis, Streptococcus pyogenes, Streptococcus pneumoniae, Enterobacter aerogenes, Escherichia coli, Haemophilus influenzae, Klebsiella pneumoniae, Neisseria gonorrhoeae, Pseudomonas aeruginosa, and Serratia marcescens.

INDICATIONS AND USAGE: Gentamicin Sulfate Ophthalmic Solution is indicated in the topical treatment of ocular bacterial infections, including conjunctivitis, keratitis, keratoconjunctivitis, corneal ulcers, blepharitis, blepharoconjunctivitis, acute meibomianitis, and dacryocystitis caused by susceptible strains of the following microorganisms: Staphylococcus aureus, Staphylococcus epidermidis, Streptococcus pyogenes, Streptococcus pneumoniae, Enterobacter aerogenes, Escherichia coli, Haemophilus influenzae, Klebsiella pneumoniae, Neisseria gonorrhoeae, Pseudomonas aeruginosa, and Serratia marcescens.

CONTRAINDICATIONS

CONTRAINDICATIONS: Gentamicin Sulfate Ophthalmic Solution is contraindicated in patients with known hypersensitivity to any of the components.

WARNINGS

WARNINGS: NOT FOR INJECTION INTO THE EYE. Gentamicin Sulfate Ophthalmic Solution is not for injection. It should never be injected subconjunctivally, nor should it be directly introduced into the anterior chamber of the eye.

PRECAUTIONS

PRECAUTIONS: General: Prolonged use of topical antibiotics may give rise to overgrowth of non-susceptible organisms including fungi. Bacterial resistance to gentamicin may also develop. If purulent discharge, inflammation or pain becomes aggravated, the patient should discontinue use of the medication and consult a physician. If irritation or hypersensitivity to any component of the drug develops, the patient should discontinue use of this preparation, and appropriate therapy should be instituted.

PATIENT COUNSELING INFORMATION

Information for Patients: To avoid contamination, do not touch tip of container to the eye, eyelid, or any surface.

CARCINOGENESIS AND MUTAGENESIS AND IMPAIRMENT OF FERTILITY

Carcinogenesis, Mutagenesis, Impairment of Fertility: There are no published carcinogenicity or impairment of fertility studies on gentamicin. Aminoglycoside antibiotics have been found to be non-mutagenic.

PREGNANCY

Pregnancy: Pregnancy Category C. Gentamicin has been shown to depress body weights, kidney weights, and median glomerular counts in newborn rats when administered systemically to pregnant rats in daily doses approximately 500 times the maximum recommended ophthalmic human dose. There are no adequate and well-controlled studies in pregnant women. Gentamicin should be used during pregnancy only if the potential benefit justifies the potential risk to the fetus.

PEDIATRIC USE

Pediatric Use: Safety and effectiveness in neonates have not been established.

ADVERSE REACTIONS

ADVERSE REACTIONS: Bacterial and fungal corneal ulcers have developed during treatment with gentamicin ophthalmic preparations. The most frequently reported adverse reactions are ocular burning and irritation upon drug instillation, non-specific conjunctivitis, conjunctival epithelial defects, and conjunctival hyperemia. Other adverse reactions which have occurred rarely are allergic reactions, thrombocytopenic purpura, and hallucinations.

DOSAGE AND ADMINISTRATION: Instill one or two drops into the affected eye(s) every four hours. In severe infections, dosage may be increased to as much as two drops once every hour.

HOW SUPPLIED

HOW SUPPLIED: Gentamicin Sulfate Ophthalmic Solution: 5 mL in plastic DROP-TAINER* dispenser. NDC 71205-333-05

STORAGE: Protect from light and store away from heat. Store at controlled room temperature 15°-25°C (59°-77°F).

To report SUSPECTED ADVERSE REACTIONS, contact Sandoz Inc., at 1-800-525-8747 or FDA at 1-800-FDA-1088 or www.fda.gov/medwatch.

*DROP-TAINER is a registered trademark of Alcon Research, Ltd.

Rx Only

9011648-0315

Manufactured by

Alcon Laboratories, Inc.

Fort Worth, Texas 76134 for

Sandoz Inc.

Princeton, NJ 08540

Relabeled by

Proficient Rx LP

Thousand Oaks, CA 91320

Rev. April 2015

PRINCIPAL DISPLAY PANEL

NDC 71205-333-05

Gentamicin

Sulfate

Ophthalmic

Solution, USP

Equivalent to 3 mg

Gentamicin per mL

Rx Only

STERILE

5 mL